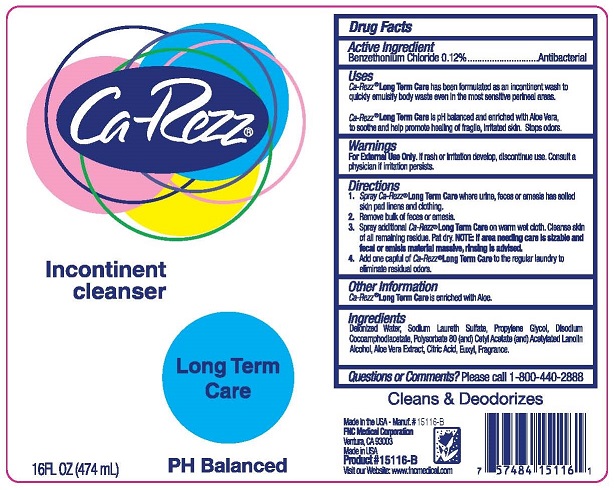 DRUG LABEL: CA-REZZ - LONG TERM CARE - INCONTINENT CLEANSER
NDC: 60762-151 | Form: SOLUTION
Manufacturer: FNC MEDICAL CORPORATION
Category: otc | Type: HUMAN OTC DRUG LABEL
Date: 20251022

ACTIVE INGREDIENTS: BENZETHONIUM CHLORIDE 0.12 g/100 mL
INACTIVE INGREDIENTS: PROPYLENE GLYCOL; DISODIUM COCOAMPHODIACETATE; POLYSORBATE 80; CETYL ACETATE; ACETYLATED LANOLIN ALCOHOLS; ALOE VERA WHOLE; SODIUM LAURETH SULFATE; ANHYDROUS CITRIC ACID; PHENOXYETHANOL; ETHYLHEXYLGLYCERIN; WATER

FNC - CA-REZZ - LONG TERM CARE - INCONTINENT CLEANSER 16 oz (60762-151)

ACTIVE INGREDIENT

BENZETHONIUM CHLORIDE 0.12%

PURPOSE

ANTIBACTERIAL

USES

CA-REZZ LONG TERM CARE WASH HAS BEEN FORMULATED AS AN INCONTINENT WASH TO QUICKLY EMULSIFY BODY WASTE EVEN IN THE MOST SENSITIVE PERINEAL AREAS.

CA-REZZ LONG TERM CARE WASH IS PH BALANCED AND ENRICHED WITH ALOE VERA, TO SOOTHE AND HELP PROMOTE HEALING OF FRAGILE, IRRITATED SKIN. STOPS ODORS.

WARNINGS

FOR EXTERNAL USE ONLY. IF RASH OR IRRITATION DEVELOP, DISCONTINUE USE. CONSULT A PHYSICIAN IF IRRITATION PERSISTS.

KEEP OUT OF REACH OF CHILDREN.

DIRECTIONS

1. SPRAY CA-REZZ LONG TERM CARE WASH WHERE URINE, FECES OR EMESIS HAS SOILED SKIN PAD LINENS AND CLOTHING.
2. REMOVE BULK OF FECES OR EMESIS.
3. SPRAY ADDITIONAL CA-REZZ LONG TERM CARE WASH ON WARM WET CLOTH. CLEANSE SKIN OF ALL REMAINING RESIDUE. PAT DRY. NOTE: IF AREA NEEDING CARE IS SIZEABLE AND FECAL OR EMESIS MATERIAL MASSIVE, RINSING IS ADVISED.
4. ADD ONE CAPFUL OF CA-REZZ LONG TERM CARE WASH TO THE REGULAR LAUNDRY TO ELIMINATE RESIDUAL ODORS.

OTHER INFORMATION

CA-REZZ NORSIC WASH IS ENRICHED WITH ALOE.

INGREDIENTS

DEIONIZED WATER, SODIUM LAURETH SULFATE, PROPYLENE GLYCOL, DISODIUM COCOAMPHODIACETATE, POLYSORBATE 80 (AND) CETYL ALCOHOL (AND) ACETYLATED LANOLIN ALCOHOL, ALOE VERA EXTRACT, CITRIC ACID, PHENOXYETHANOL, ETHYHEXYLGLYCERIN, D&C YELLOW #10, FRAGRANCE.

QUESTIONS OR COMMENTS?

PLEASE CALL 1-800-440-2888